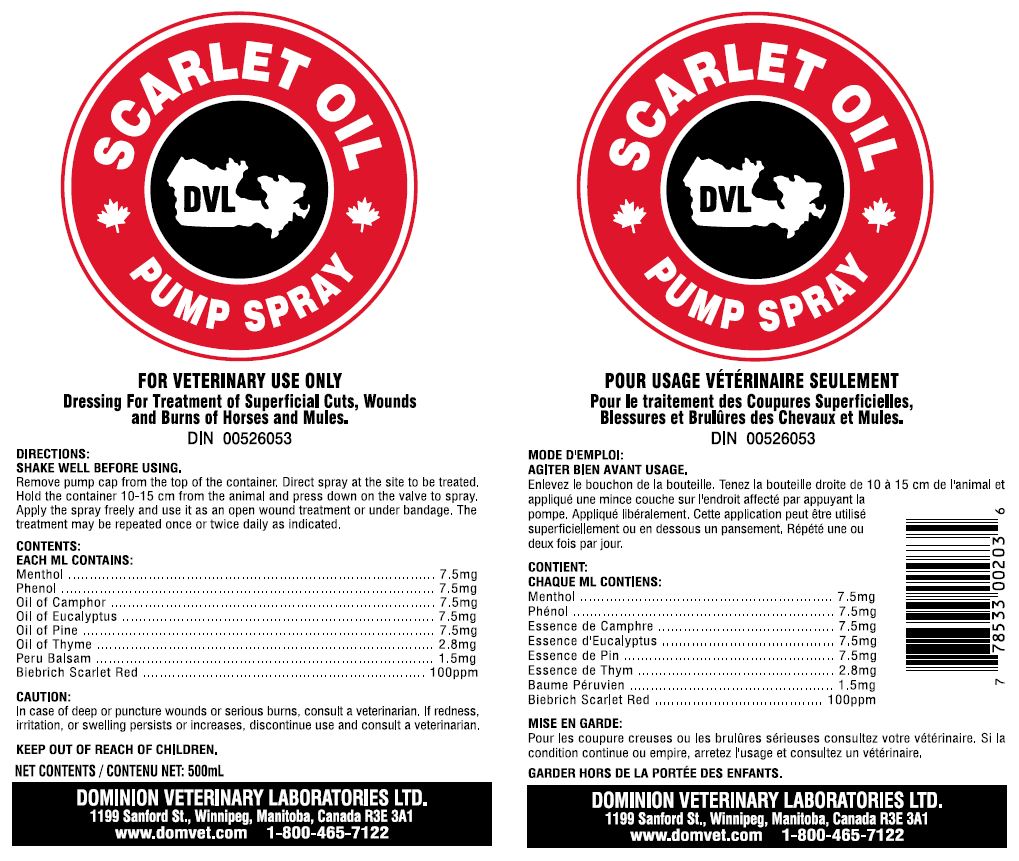 DRUG LABEL: SCARLET
NDC: 64120-108 | Form: OIL
Manufacturer: DOMINION VETERINARY LABORATORIES LTD.
Category: animal | Type: OTC ANIMAL DRUG LABEL
Date: 20211110

ACTIVE INGREDIENTS: MENTHOL 7.5 mg/1 mL; PHENOL 7.5 mg/1 mL; CAMPHOR OIL 7.5 mg/1 mL; EUCALYPTUS OIL 7.5 mg/1 mL; WHITE PINE OIL 7.5 mg/1 mL; THYME OIL 2.8 mg/1 mL; BALSAM PERU OIL 1.5 mg/1 mL; SOLVENT RED 24 0.1 mg/1 mL

DOMINION VETERINARY LABORATORIES - SCARLET OIL PUMP SPRAY

INDICATIONS:

DRESSING FOR TREATMENT OF SUPERFICIAL CUTS, WOUNDS, AND BURNS OF HORSES AND MULES.